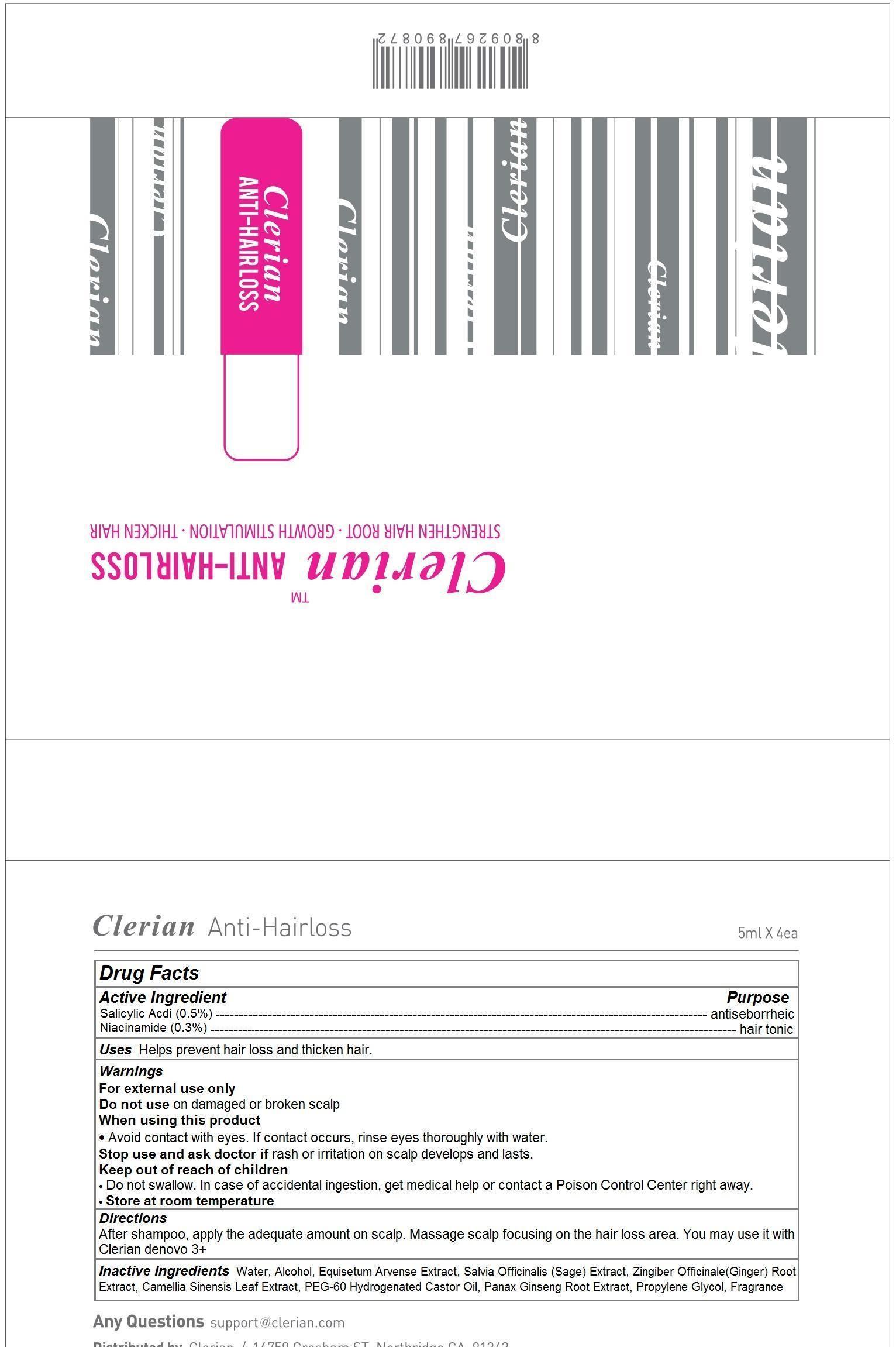 DRUG LABEL: Clerian Anti-Hairloss
NDC: 69767-101 | Form: LIQUID
Manufacturer: CLERIAN, INC.
Category: otc | Type: HUMAN OTC DRUG LABEL
Date: 20150507

ACTIVE INGREDIENTS: SALICYLIC ACID 0.5 1/5 mL; NIACINAMIDE 0.3 1/5 mL
INACTIVE INGREDIENTS: WATER; ALCOHOL; EQUISETUM ARVENSE BRANCH; SALVIA OFFICINALIS WHOLE; GINGER; GREEN TEA LEAF; PEG-60 HYDROGENATED CASTOR OIL; ASIAN GINSENG; PROPYLENE GLYCOL

Clerian Anti-Hairloss